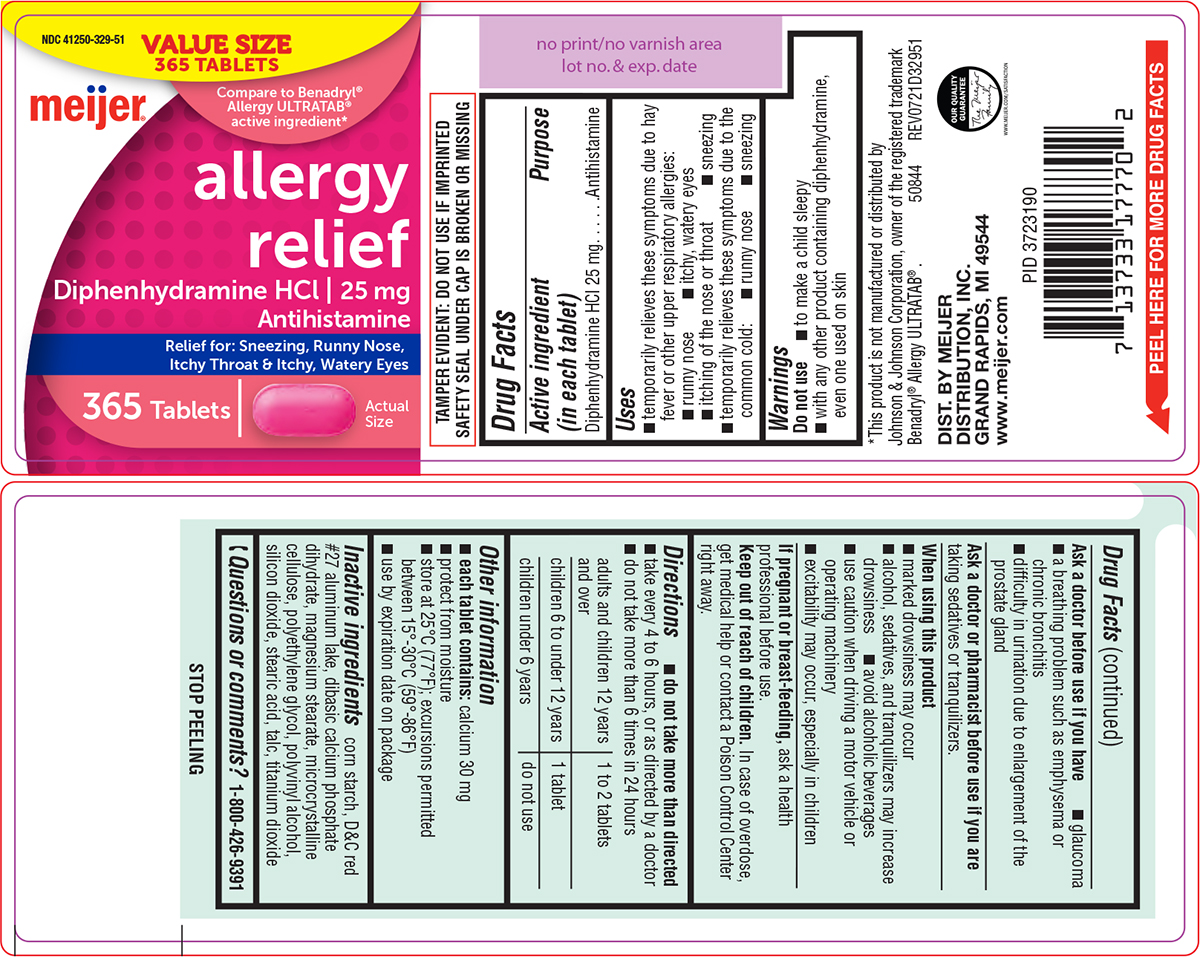 DRUG LABEL: Allergy Relief
NDC: 41250-329 | Form: TABLET, FILM COATED
Manufacturer: Meijer Distribution Inc
Category: otc | Type: HUMAN OTC DRUG LABEL
Date: 20240820

ACTIVE INGREDIENTS: DIPHENHYDRAMINE HYDROCHLORIDE 25 mg/1 1
INACTIVE INGREDIENTS: STARCH, CORN; D&C RED NO. 27 ALUMINUM LAKE; DIBASIC CALCIUM PHOSPHATE DIHYDRATE; MAGNESIUM STEARATE; MICROCRYSTALLINE CELLULOSE; POLYETHYLENE GLYCOL, UNSPECIFIED; POLYVINYL ALCOHOL, UNSPECIFIED; SILICON DIOXIDE; STEARIC ACID; TALC; TITANIUM DIOXIDE

Meijer 44-329-Delisted

Active ingredient (in each tablet)

Diphenhydramine HCl 25 mg

Purpose

Antihistamine

Uses

- temporarily relieves these symptoms due to hay fever or other upper respiratory allergies:
  - runny nose
  - itchy, watery eyes
  - itching of the nose or throat
  - sneezing
- temporarily relieves these symptoms due to the common cold:
  - runny nose
  - sneezing

Warnings

Do not use

- to make a child sleepy
- with any other product containing diphenhydramine, even one used on skin

Ask a doctor before use if you have

- glaucoma
- a breathing problem such as emphysema or chronic bronchitis
- difficulty in urination due to enlargement of the prostate gland

Ask a doctor or pharmacist before use if you are

taking sedatives or tranquilizers.

When using this product

- marked drowsiness may occur
- alcohol, sedatives, and tranquilizers may increase drowsiness
- avoid alcoholic beverages
- use caution when driving a motor vehicle or operating machinery
- excitability may occur, especially in children

If pregnant or breast-feeding,

ask a health professional before use.

Keep out of reach of children.

In case of overdose, get medical help or contact a Poison Control Center right away.

Directions

- do not take more than directed
- take every 4 to 6 hours, or as directed by a doctor
- do not take more than 6 times in 24 hours

adults and children 12 years and over | 1 to 2 tablets
children 6 to under 12 years | 1 tablet
children under 6 years | do not use

Other information

- each tablet contains: calcium 30 mg
- protect from moisture
- store at 25°C (77°F); excursions permitted between 15°-30°C (59°-86°F)
- use by expiration date on package

Inactive ingredients

corn starch, D&C red #27 aluminum lake, dibasic calcium phosphate dihydrate, magnesium stearate, microcrystalline cellulose, polyethylene glycol, polyvinyl alcohol, silicon dioxide, stearic acid, talc, titanium dioxide

Questions or comments?

1-800-426-9391

Principal Display Panel

VALUE SIZE
365 TABLETS

NDC 41250-329-51

Compare to Benadryl®
Allergy ULTRATAB®
active ingredient*

meijer®

allergy
relief

Diphenhydramine HCl | 25 mg
Antihistamine

Relief for: Sneezing, Runny Nose,
Itchy Throat & Itchy, Watery Eyes

365 Tablets

Actual
Size

TAMPER EVIDENT: DO NOT USE IF IMPRINTED
SAFETY SEAL UNDER CAP IS BROKEN OR MISSING

*This product is not manufactured or distributed by
Johnson & Johnson Corporation, owner of the registered trademark
Benadryl® Allergy ULTRATAB® . 50844 REV0721D32951

DIST. BY MEIJER
DISTRIBUTION, INC.
GRAND RAPIDS, MI 49544
www.meijer.com

Meijer L-1214-329-51-UPCR REV0721D